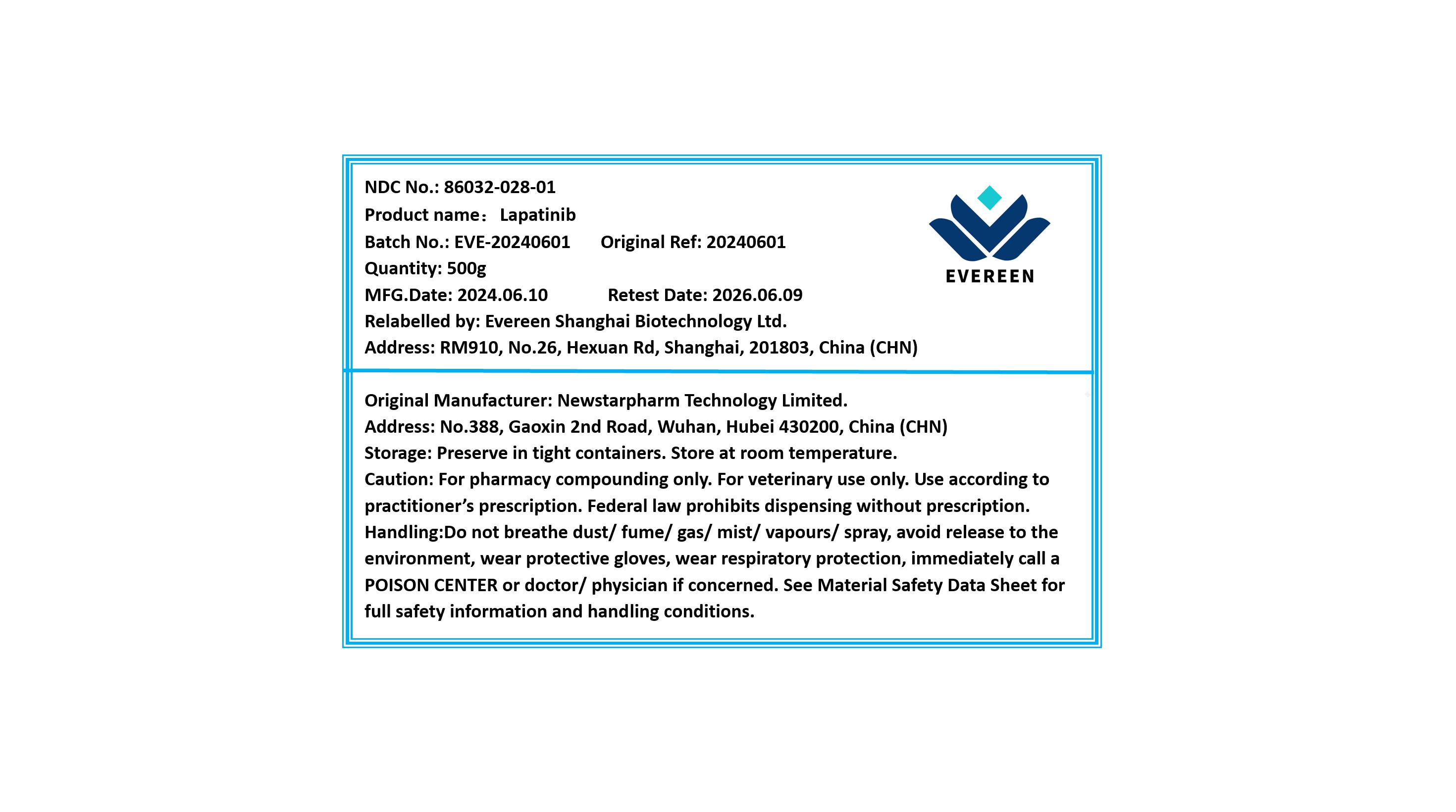 DRUG LABEL: Lapatinib
NDC: 86032-028 | Form: POWDER
Manufacturer: Evereen Shanghai Biotechnology Ltd.
Category: other | Type: BULK INGREDIENT - ANIMAL DRUG
Date: 20240904

ACTIVE INGREDIENTS: LAPATINIB 1 g/1 g

Lapatinib